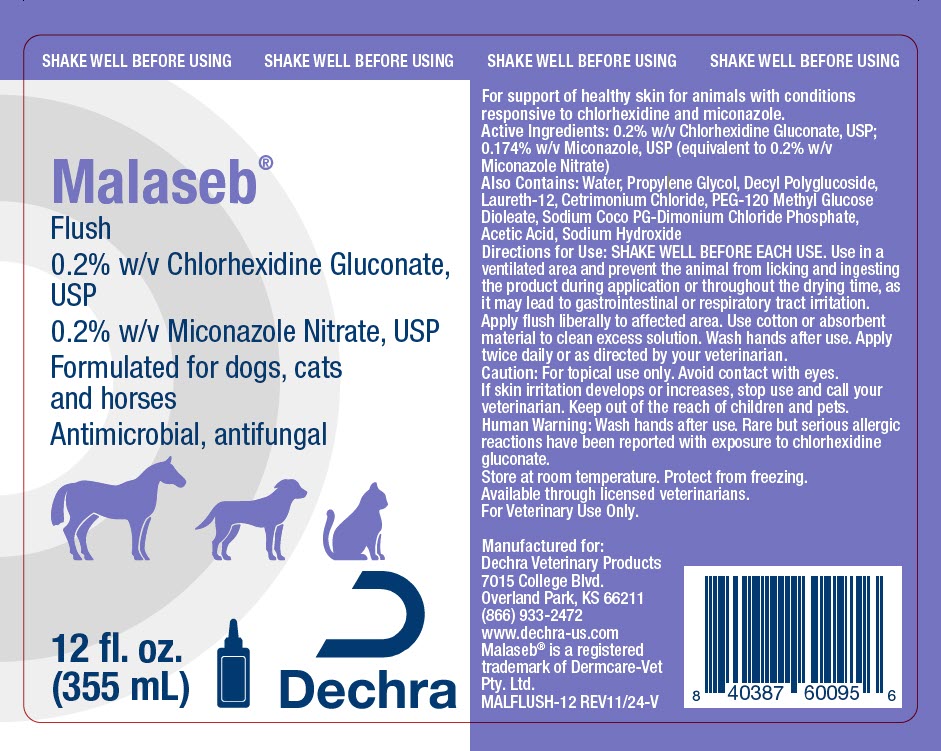 DRUG LABEL: Malaseb Flush
NDC: 17033-187 | Form: SOLUTION
Manufacturer: Dechra Veterinary Products
Category: animal | Type: OTC ANIMAL DRUG LABEL
Date: 20241212

ACTIVE INGREDIENTS: CHLORHEXIDINE GLUCONATE 2 mg/1 mL; MICONAZOLE NITRATE 2 mg/1 mL

Malaseb® Flush

VETERINARY INDICATIONS

For support of healthy skin for animals with conditions responsive to chlorhexidine and miconazole.

DESCRIPTION

Active Ingredients: 0.2% w/v Chlorhexidine Gluconate, USP; 0.174% w/v Miconazole, USP (equivalent to 0.2% w/v Miconazole Nitrate)

Also Contains: Water, Propylene Glycol, Decyl Polyglucoside, Laureth-12, Cetrimonium Chloride, PEG-120 Methyl Glucose Dioleate, Sodium Coco PG-Dimonium Chloride Phosphate, Acetic Acid, Sodium Hydroxide

DOSAGE AND ADMINISTRATION

Directions for Use: SHAKE WELL BEFORE EACH USE. Use in a ventilated area and prevent the animal from licking and ingesting the product during application or throughout the drying time, as it may lead to gastrointestinal or respiratory tract irritation.

Apply flush liberally to affected area. Use cotton or absorbent material to clean excess solution. Wash hands after use. Apply twice daily or as directed by your veterinarian.

PRECAUTIONS

Caution: For topical use only. Avoid contact with eyes. If skin irritation develops or increases, stop use and call your veterinarian. Keep out of the reach of children and pets.

SAFE HANDLING WARNING

Human Warning: Wash hands after use. Rare but serious allergic reactions have been reported with exposure to chlorhexidine gluconate.

STORAGE AND HANDLING

Store at room temperature. Protect from freezing.

Available through licensed veterinarians.

For Veterinary Use Only.

Manufactured for:
Dechra Veterinary Products
7015 College Blvd.
Overland Park, KS 66211
(866) 933-2472

www.dechra-us.com
Malaseb® is a registered
trademark of Dermcare-Vet
Pty. Ltd.

MALFLUSH-12 REV11/24-V

PRINCIPAL DISPLAY PANEL - 355 mL Bottle Label

SHAKE WELL BEFORE USING

Malaseb®
Flush
0.2% w/v Chlorhexidine Gluconate,
USP
0.2% w/v Miconazole Nitrate, USP
Formulated for dogs, cats
and horses
Antimicrobial, antifungal

12 fl. oz.
(355 mL)

Dechra